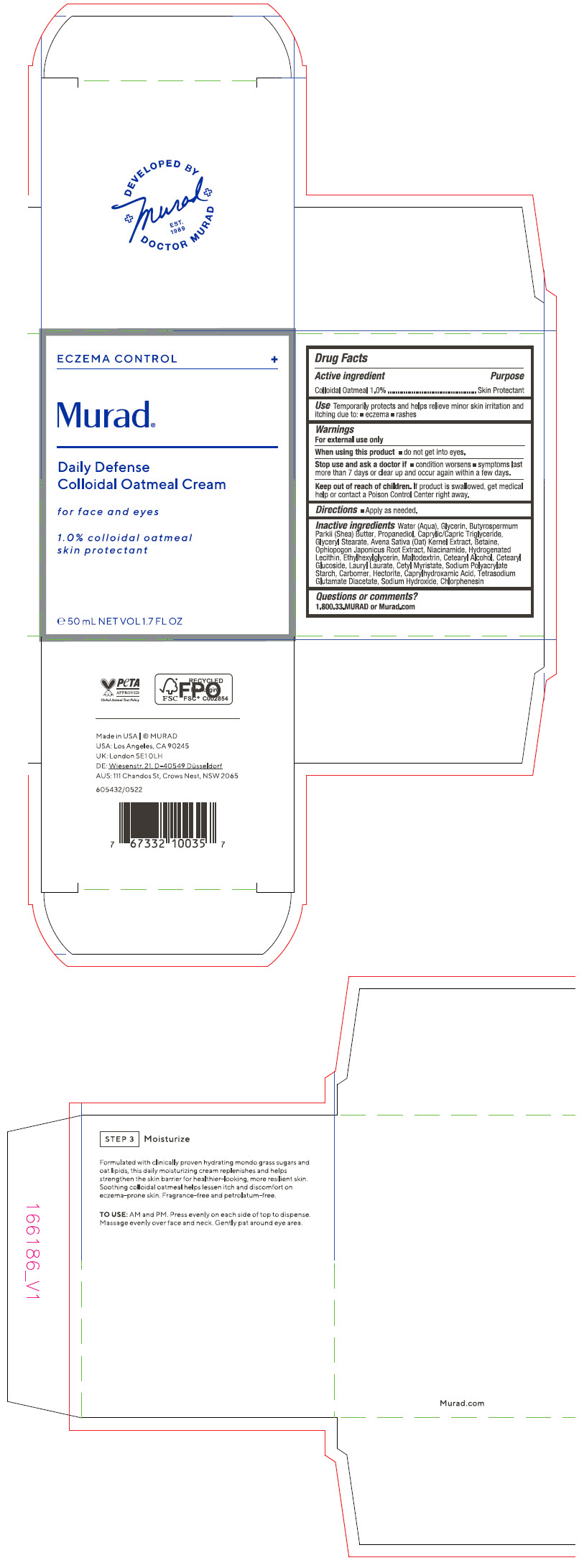 DRUG LABEL: Daily Defense Colloidal Oatmeal 
NDC: 70381-122 | Form: CREAM
Manufacturer: Murad, LLC
Category: otc | Type: HUMAN OTC DRUG LABEL
Date: 20220615

ACTIVE INGREDIENTS: OATMEAL 1 g/100 mL
INACTIVE INGREDIENTS: WATER; GLYCERIN; SHEA BUTTER; PROPANEDIOL; MEDIUM-CHAIN TRIGLYCERIDES; GLYCERYL MONOSTEARATE; OAT; BETAINE; OPHIOPOGON JAPONICUS ROOT; NIACINAMIDE; HYDROGENATED SOYBEAN LECITHIN; ETHYLHEXYLGLYCERIN; MALTODEXTRIN; CETOSTEARYL ALCOHOL; CETEARYL GLUCOSIDE; LAURYL LAURATE; CETYL MYRISTATE; HECTORITE; CAPRYLHYDROXAMIC ACID; TETRASODIUM GLUTAMATE DIACETATE; SODIUM HYDROXIDE; CHLORPHENESIN; CARBOMER HOMOPOLYMER, UNSPECIFIED TYPE; SODIUM POLYACRYLATE STARCH (25 MICROMETER PARTICLE)

Daily Defense Colloidal Oatmeal Cream
for face and eyes

Drug Facts

Active ingredient

Colloidal Oatmeal 1.0%

Purpose

Skin Protectant

Use

Temporarily protects and helps relieve minor skin irritation and itching due to:

- eczema
- rashes

Warnings

For external use only

When using this product

- do not get into eyes.

Stop use and ask a doctor if

- condition worsens
- symptoms last more than 7 days or clear up and occur again within a few days.

Keep out of reach of children. If swallowed, get medical help or contact a Poison Control Center right away.

Directions

- Apply as needed.

Inactive ingredients

Water (Aqua), Glycerin, Butyrospermum Parkii (Shea) Butter, Propanediol, Caprylic/Capric Triglyceride, Glyceryl Stearate, Avena Sativa (Oat) Kernel Extract, Betaine, Ophiopogon Japonicus Root Extract, Niacinamide, Hydrogenated Lecithin, Ethylhexylglycerin, Maltodextrin, Cetearyl Alcohol, Cetearyl Glucoside, Lauryl Laurate, Cetyl Myristate, Sodium Polyacrylate Starch, Carbomer, Hectorite, Caprylhydroxamic Acid, Tetrasodium Glutamate Diacetate, Sodium Hydroxide, Chlorphenesin

Questions or comments?

1.800.33.MURAD or Murad.com

PRINCIPAL DISPLAY PANEL - 50 mL Bottle Carton

ECZEMA CONTROL
+

Murad®

Daily Defense
Colloidal Oatmeal Cream

for face and eyes

1.0% colloidal oatmeal
skin protectant

℮ 50 mL NET VOL 1.7 FL OZ